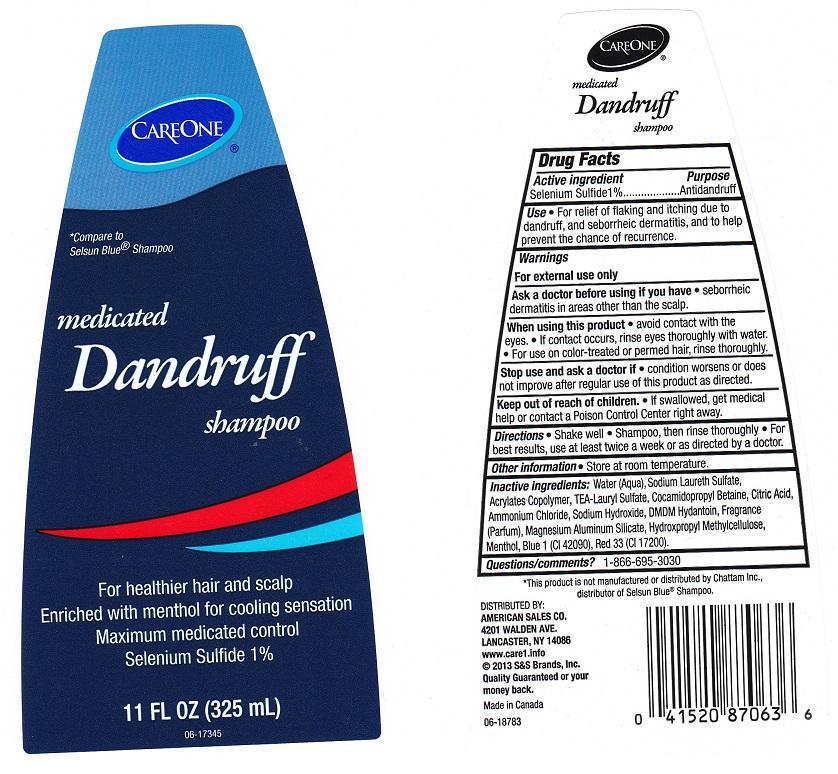 DRUG LABEL: CARE ONE
NDC: 41520-620 | Form: LIQUID
Manufacturer: AMERICAN SALES COMPANY
Category: otc | Type: HUMAN OTC DRUG LABEL
Date: 20130715

ACTIVE INGREDIENTS: SELENIUM SULFIDE 10 mg/1 mL
INACTIVE INGREDIENTS: WATER; SODIUM LAURETH SULFATE; METHACRYLIC ACID - METHYL METHACRYLATE COPOLYMER (1:1); TEA-LAURYL SULFATE; COCAMIDOPROPYL BETAINE; CITRIC ACID MONOHYDRATE; AMMONIUM CHLORIDE; SODIUM HYDROXIDE; DMDM HYDANTOIN; MAGNESIUM ALUMINUM SILICATE; HYPROMELLOSES; MENTHOL; FD&C BLUE NO. 1; D&C RED NO. 33

DRUG FACTS

ACTIVE INGREDIENT

SELENIUM SULFIDE 1%

PURPOSE

ANTIDANDRUFF

USE

FOR RELIEF OF FLAKING AND ITCHING DUE TO DANDRUFF, AND SEBORRHEIC DERMATITIS, AND TO HELP PREVENT THE CHANCE OF RECURRENCE.

WARNINGS

FOR EXTERNAL USE ONLY.

ASK A DOCTOR BEFORE USING IF YOU HAVE

SEBORRHEIC DERMATITIS IN AREAS OTHER THAN THE SCALP.

WHEN USING THIS PRODUCT

AVOID CONTACT WITH THE EYES. IF CONTACT OCCURS, RINSE EYES THOROUGHLY WITH WATER. FOR USE ON COLOR-TREATED OR PERMED HAIR, RINSE THOROUGHLY.

STOP USE AND ASK A DOCTOR IF

CONDITION WORSENS OR DOES NOT IMPROVE AFTER REGULAR USE OF THIS PRODUCT AS DIRECTED.

KEEP OUT OF REACH OF CHILDREN

IF SWALLOWED, GET MEDICAL HELP OR CONTACT A POISON CONTROL CENTER RIGHT AWAY.

DIRECTIONS

SHAKE WELL. SHAMPOO, THEN RINSE THOROUGHLY. FOR BEST RESULTS, USE AT LEAST TWICE A WEEK OR AS DIRECTED BY A DOCTOR.

OTHER INFORMATION

STORE AT ROOM TEMPERATURE.

INACTIVE INGREDIENTS:

WATER (AQUA), SODIUM LAURETH SULFATE, ACRYLATES COPOLYMER, TEA-LAURYL SULFATE, COCAMIDOPROPYL BETAINE, CITRIC ACID, AMMONIUM CHLORIDE, SODIUM HYDROXIDE, DMDM HYDANTOIN, FRAGRANCE (PARFUM), MAGNESIUM ALUMINUM SILICATE, HYDROXYPROPYL METHYLCELLULOSE, MENTHOL, BLUE 1 (CI 42090), RED 33 (CI 17200).

QUESTIONS/COMMENTS?

1-866-695-3030